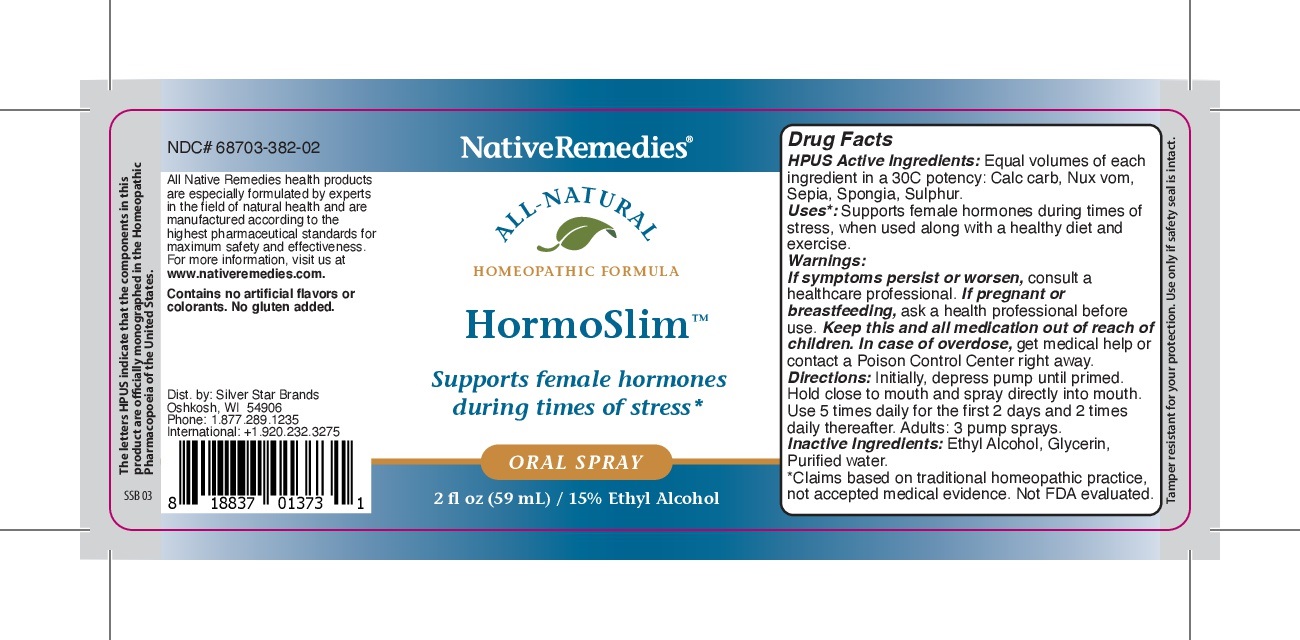 DRUG LABEL: Hormoslim
NDC: 68703-382 | Form: SPRAY
Manufacturer: Silver Star Brands
Category: homeopathic | Type: HUMAN OTC DRUG LABEL
Date: 20250101

ACTIVE INGREDIENTS: SEPIA OFFICINALIS JUICE 30 [hp_C]/59 mL; SPONGIA OFFICINALIS SKELETON, ROASTED 30 [hp_C]/59 mL; SULFUR 30 [hp_C]/59 mL; STRYCHNOS NUX-VOMICA SEED 30 [hp_C]/59 mL; CALCIUM CARBONATE 30 [hp_C]/59 mL
INACTIVE INGREDIENTS: ALCOHOL; GLYCERIN; WATER

NativeRemedies HormoSlim

HPUS Active Ingredients: Equal volumse of each ingredient in 30C potency: Calc carb, Nux vom, Sepia, Spongia, Sulphur.

Uses*:

Uses*: Supports female hormones during times of stress, when used along with a healthy diet and excercise.

*Claims based on traditional homeopathic practice, not accepted medical evidence. Not FDA evaluated.

Warnings

Warnings: If symptoms persis or worsen, consulta healthcare professional. if pregnant or breastfeeding, ask a health professional before use. Keep this and all medication out of reach of children. in case of overdose, get medical help or contact a Poison Control Center right away.

Directions

Directions: Intially, depress pump until primed. Hold close to mouth and spray directly into mouth. Use 5 times daily for the first 2 days and 2 times dailly therafer. Adults: 3 pump sprays.

OTHER SAFETY INFORMATION

Contains no artificial flavors or colorants. No gluten added.

Tamper resistant for your protection. use only if saftey seal is intact.

Inactive Ingredients

Inactive Ingredients: Ethyl Alcohol, Glycerin, Purified water.

KEEP OUT OF REACH OF CHILDREN

Keep this and all meidcation out of recach of children.

PREGNANCY OR BREAST FEEDING

If pregnant or breastfeeding, ask a health professional before use.

PURPOSE

Supports female hormones during times of stress*

*Claims based on traditinoal homeopathic practice, not accepted medical evidence. Not FDA regulated.